DRUG LABEL: Quik Spray
NDC: 41900-500 | Form: SPRAY
Manufacturer: Cinogen Cosmetics Zhaoqing, LTD.
Category: otc | Type: HUMAN OTC DRUG LABEL
Date: 20090904

ACTIVE INGREDIENTS: ALCOHOL 0.62 mL/1 mL; TRICLOSAN 0.03 mL/1 mL
INACTIVE INGREDIENTS: ALOE VERA LEAF; WATER; HYDROXYETHYL CELLULOSE (140 CPS AT 5%); POLYOXYL 40 HYDROGENATED CASTOR OIL; PROPYLENE GLYCOL; ALPHA-TOCOPHEROL

QuikSpray Advanced Hand Sanitizing Spray

Drug Facts

Active Ingredients Purpose

Ethyl Alcohol 62 percent Antimicrobial

Triclosan 0.3 percent Antimicrobial

Uses

For hand washing to decrease bacteria on the skin,

recommended for repeated use.

Warnings

For external use on the hands only. Flammable.

Keep away from heat and flame. Keep out if reach of children.

Stop use and ask doctor if irritation develops.

Directions

Wet hands thoroughly with product and allow to dry without wiping.

Not recommended for infants.

INACTIVE INGREDIENT

Aloe Barbadensis Extract , Deionized Water , Hydroxyehylcellulose , PEG 40 Hydrogenated Castor Oil ,

Perfume , Propylene Glycol , Tocopherol

DESCRIPTION

Net Wt 8mL 0.27 FL OZ Made in China

Dist by Nupak, LLC 5823 Bowen Daniek Dr. 1601 Tampa FL 33616 1 888 988 7232

PACKAGE LABEL

6 Hour Germ Protection

QuikSpray

90 plus sprays

Advanced Hand Sanitizing Spray

www.myquikspray.net

Contains Aloes Vera and Vitamin E

Kills 99.99 percent of germs